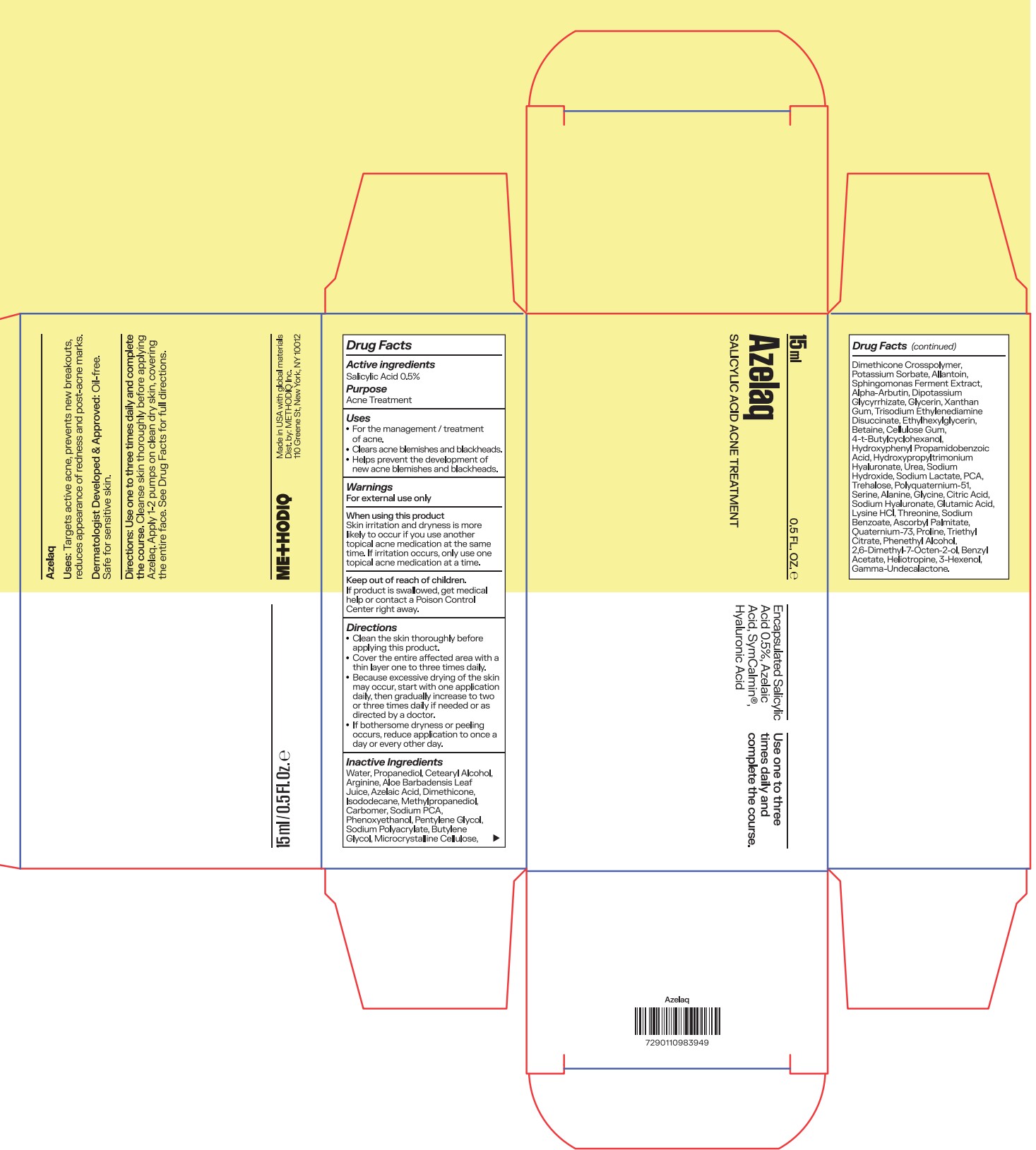 DRUG LABEL: Azelaq
NDC: 87110-003 | Form: GEL
Manufacturer: METHODIQ INC.
Category: otc | Type: HUMAN OTC DRUG LABEL
Date: 20251110

ACTIVE INGREDIENTS: SALICYLIC ACID 5 mg/1 mL
INACTIVE INGREDIENTS: PHENOXYETHANOL; DIMETHICONE CROSSPOLYMER (450000 MPA.S AT 12% IN CYCLOPENTASILOXANE); POLYQUATERNIUM-51 (2-METHACRYLOYLOXYETHYL PHOSPHORYLCHOLINE/N-BUTYL METHACRYLATE; 3:7); BENZYL ACETATE; UREA; TREHALOSE; SODIUM LACTATE; PENTYLENE GLYCOL; SODIUM POLYACRYLATE (8000 MW); MICROCRYSTALLINE CELLULOSE; ALLANTOIN; DIPOTASSIUM GLYCYRRHIZATE; THREONINE; WATER; GLYCINE; LYSINE HCL; 3-HEXENOL; SODIUM BENZOATE; QUATERNIUM-73; PROLINE; BETAINE; PHENETHYL ALCOHOL; CELLULOSE GUM; TRIETHYL CITRATE; ETHYLHEXYLGLYCERIN; 4-T-BUTYLCYCLOHEXANOL; PROPANEDIOL; AZELAIC ACID; SODIUM PCA; BUTYLENE GLYCOL; HYDROXYPHENYL PROPAMIDOBENZOIC ACID; ALANINE; GLUTAMIC ACID; ASCORBYL PALMITATE; GAMMA-UNDECALACTONE; CETEARYL ALCOHOL; CARBOMER; ALOE BARBADENSIS LEAF JUICE; ISODODECANE; GLYCERIN; TRISODIUM ETHYLENEDIAMINE DISUCCINATE; SERINE; CITRIC ACID; 2,6-DIMETHYL-7-OCTEN-2-OL; HELIOTROPINE; ALPHA-ARBUTIN; XANTHAN GUM; DIMETHICONE; METHYLPROPANEDIOL; ARGININE; POTASSIUM SORBATE; PCA; SODIUM HYALURONATE; SODIUM HYDROXIDE

Azelaq

Active ingredients

Salicylic Acid 0.5%

Purpose

Salicylic Acid 0.5%..............Acne Treatment

Uses

- For the management / treatment of acne.
- Clears acne blemishes and blackheads.
- Helps prevent the development of new acne blemishes and blackheads.

Warnings

For external use only

When using this product
Skin irritation and dryness is more likely to occur if you use another topical acne medication at the same time. If irritation occurs, only use one topical acne medication at a time.

Keep out of reach of children.
If product is swallowed, get medical help or contact a Poison Control Center right away.

Directions

- Clean the skin thoroughly before applying this product.
- Cover the entire affected area with a thin layer one to three times daily.
- Because excessive drying of the skin may occur, start with one application daily, then gradually increase to two or three times daily if needed or as directed by a doctor.
- If bothersome dryness or peeling occurs, reduce application to once a day or every other day.

Inactive ingredients

Water, Propanediol, Cetearyl Alcohol, Arginine, Aloe Barbadensis Leaf Juice, Azelaic Acid, Dimethicone, Isododecane, Methylpropanediol, Carbomer, Sodium PCA, Phenoxyethanol, Pentylene Glycol, Sodium Polyacrylate, Butylene Glycol, Microcrystalline Cellulose, Dimethicone Crosspolymer, Potassium Sorbate, Allantoin, Sphingomonas Ferment Extract, Alpha-Arbutin, Dipotassium Glycyrrhizate, Glycerin, Xanthan Gum, Trisodium Ethylenediamine Disuccinate, Ethylhexylglycerin, Betaine, Cellulose Gum, 4-t-Butylcyclohexanol, Hydroxyphenyl Propamidobenzoic Acid, Hydroxypropyltrimonium Hyaluronate, Urea, Sodium Hydroxide, Sodium Lactate, PCA, Trehalose, Polyquaternium-51, Serine, Alanine, Glycine, Citric Acid, Sodium Hyaluronate, Glutamic Acid, Lysine HCl, Threonine, Sodium Benzoate, Ascorbyl Palmitate, Quaternium-73, Proline, Triethyl Citrate, Phenethyl Alcohol, 2,6-Dimethyl-7-Octen-2-ol, Benzyl Acetate, Heliotropine, 3-Hexenol, Gamma-Undecalactone.

PACKAGE LABEL

15ml

0.5 Fl. Oz.

Azelaq

Salicylic Acid Acne Treatment